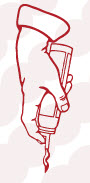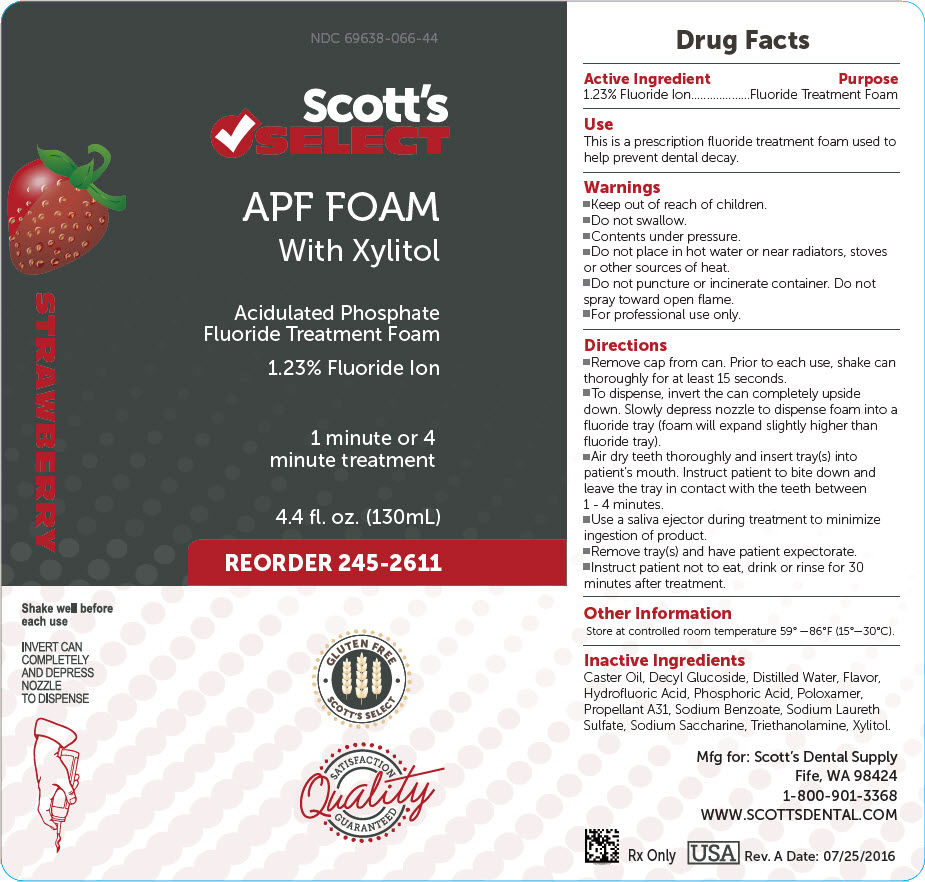 DRUG LABEL: Scotts Select APF Foam Fluoride
NDC: 69638-066 | Form: AEROSOL, FOAM
Manufacturer: Scott's Dental Supply LLC
Category: prescription | Type: HUMAN PRESCRIPTION DRUG LABEL
Date: 20200303

ACTIVE INGREDIENTS: SODIUM FLUORIDE 0.0123 g/1 mL
INACTIVE INGREDIENTS: CASTOR OIL; DECYL GLUCOSIDE; WATER; HYDROFLUORIC ACID; PHOSPHORIC ACID; SODIUM BENZOATE; SODIUM LAURETH-3 SULFATE; SACCHARIN SODIUM; XYLITOL; POLOXAMER 407; TROLAMINE

Scott's
SELECT
APF FOAM

Drug Facts

Active Ingredient | Purpose
1.23% Fluoride Ion | Fluoride Treatment Foam

Use

This is a prescription fluoride treatment foam used to help prevent dental decay.

Warnings

- Keep out of reach of children.
- Do not swallow.
- Contents under pressure.
- Do not place in hot water or near radiators, stoves or other sources of heat.
- Do not puncture or incinerate container. Do not spray toward open flame.
- For professional use only.

Directions

- Remove cap from can. Prior to each use, shake can thoroughly for at least 15 seconds.
- To dispense, invert the can completely upside down. Slowly depress nozzle to dispense foam into a fluoride tray (foam will expand slightly higher than fluoride tray).
- Air dry teeth thoroughly and insert tray(s) into patient's mouth. Instruct patient to bite down and leave the tray in contact with the teeth between 1 - 4 minutes.
- Use a saliva ejector during treatment to minimize ingestion of product.
- Remove tray(s) and have patient expectorate.
- Instruct patient not to eat, drink or rinse for 30 minutes after treatment.

Other Information

Store at controlled room temperature 59° –86°F (15°–30°C).

Inactive Ingredients

Caster Oil, Decyl Glucoside, Distilled Water, Flavor, Hydrofluoric Acid, Phosphoric Acid, Poloxamer, Propellant A31, Sodium Benzoate, Sodium Laureth Sulfate, Sodium Saccharine, Triethanolamine, Xylitol.

STRAWBERRY

Shake well before each use

INVERT CAN COMPLETELY AND DEPRESS NOZZLE TO DISPENSE

Mfg for: Scott's Dental Supply
Fife, WA 98424
1-800-901-3368
WWW.SCOTTSDENTAL.COM

Rx Only
USA
Rev. A Date: 07/25/2016

PRINCIPAL DISPLAY PANEL - 130 mL Bottle Label

NDC 69638-066-44

Scott's
SELECT

APF FOAM
With Xylitol

Acidulated Phosphate
Fluoride Treatment Foam

1.23% Fluoride Ion

1 minute or 4
minute treatment

4.4 fl. oz. (130mL)

REORDER 245-2611

GLUTEN FREE
SCOTT'S SELECT

SATISFACTION
Quality
GUARANTEED